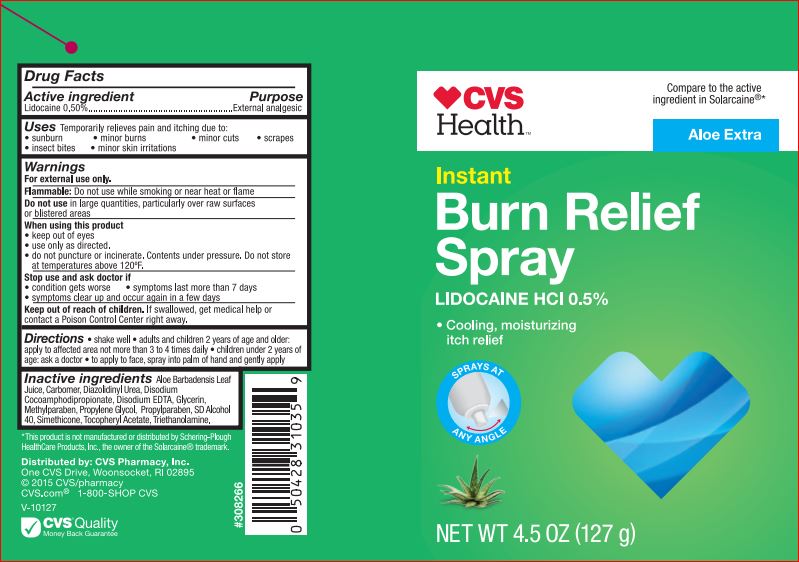 DRUG LABEL: Instant Burn Relief Aloe Extra
NDC: 59779-230 | Form: SPRAY
Manufacturer: CVS
Category: otc | Type: HUMAN OTC DRUG LABEL
Date: 20171130

ACTIVE INGREDIENTS: LIDOCAINE .50 g/100 g
INACTIVE INGREDIENTS: ALOE VERA LEAF; ALCOHOL; PROPYLENE GLYCOL; GLYCERIN; .ALPHA.-TOCOPHEROL ACETATE; TROLAMINE; DIAZOLIDINYL UREA; METHYLPARABEN; PROPYLPARABEN; DISODIUM COCOAMPHODIPROPIONATE; EDETATE DISODIUM

Actives

Lidocaine USP .50%

Purpose

External analgesic

Uses

Temporarily relieves pain and itching due to:

- sunburn
- minor burns
- scrapes
- insect bites
- minor irritations

Warnings

For external use only.

Flammable: Do not use while smoking or near heat or flame

Do not use

in large quantities, particularly over raw surfaces or blistered areas

When using this product

- keep out of eyes
- use only as directed
- do not puncture or incinerate. Contents under pressure. Do not store at temperatures above 120F

Stop use and ask a doctor if

- conditions gets worse
- symptoms last more than 7 days
- symptoms clear up and occur again in a few days

Keep out of reach of children.

If swallowed, get medical help or contact a Poison Control Center right away.

Directions

- shake well
- adults and children 2 years of age and older: apply to affected area not more than 3-4 times daily
- children under 2 years of age: ask a doctor
- to apply to face, spray into palm of hand and gently apply

Inactive ingredients

Aloe Barbadensis Leaf Juice, SD Alcohol 40, Propylene Glycol, Glycerin, Simethicone, Tocopheryl Acetate (Vitamin E Acetate), Triethanolamine, Carbomer, Diazolidinyl Urea, Methylparaben, Propylparaben, Disodium Cocoamphodipropionate, Disodium EDTA.

PACKAGE LABEL

CVS

pharmacy

INSTANT

BURN RELIEF

SPRAY

ALOE EXTRA

- instant pain relief with Lidocaine
- Cooling, moisturizing itch relief

Net WT 4.5 OZ (127g)